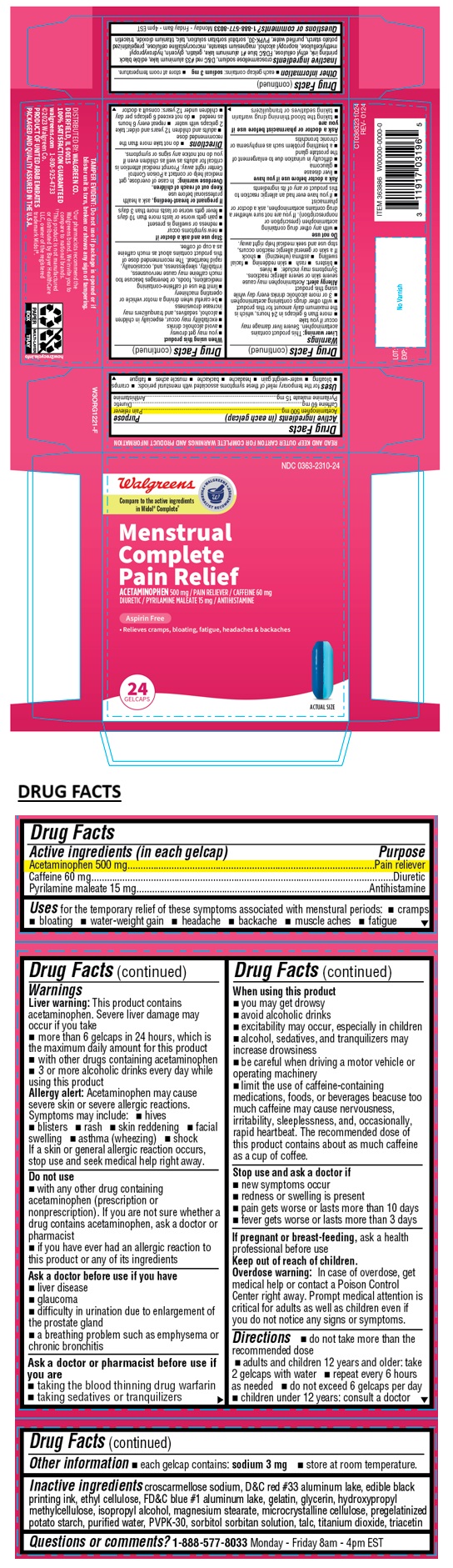 DRUG LABEL: Acetaminophen 500mg Caffeine 60mg Pyrilamine maleate 15mg
NDC: 0363-2310 | Form: TABLET
Manufacturer: WALGREENS CO.
Category: otc | Type: HUMAN OTC DRUG LABEL
Date: 20241225

ACTIVE INGREDIENTS: ACETAMINOPHEN 500 mg/1 1; CAFFEINE 60 mg/1 1; PYRILAMINE MALEATE 15 mg/1 1
INACTIVE INGREDIENTS: CROSCARMELLOSE SODIUM; D&C RED NO. 33 ALUMINUM LAKE; ETHYLCELLULOSE, UNSPECIFIED; FD&C BLUE NO. 1 ALUMINUM LAKE; GELATIN, UNSPECIFIED; GLYCERIN; HYPROMELLOSE, UNSPECIFIED; ISOPROPYL ALCOHOL; MAGNESIUM STEARATE; MICROCRYSTALLINE CELLULOSE; STARCH, POTATO; WATER; POVIDONE K30; SORBITOL; SORBITAN; TALC; TITANIUM DIOXIDE; TRIACETIN

Walgreens Menstrual Complete Pain Relief
Acetaminophen 500mg, Caffeine 60mg, Pyrilamine Maleate 15mg

Active ingredients

Acetaminophen 500mg

Caffeine 60mg

Pyrilamine maleate 15mg

Purpose

Pain reliever

Diuretic

Antihistamine

Uses

for the temporary relief of these symptoms associated with menstural periods: • cramps • bloating • water-weight gain • headache • backache • muscle aches • fatigue

Warnings

Liver warning: This product contains acetaminophen. Severe liver damage may occur if you take
• more than 6 gelcaps in 24 hours, which is the maximum daily amount for this product
• with other drugs containing acetaminophen
• 3 or more alcoholic drinks every day while using this product
Allergy alert: Acetaminophen may cause severe skin or severe allergic reactions.
Symptoms may include: • hives • blisters • rash • skin reddening • facial swelling • asthma (wheezing) • shock
If a skin or general allergic reaction occurs, stop use and seek medical help right away.

Do not use
• with any other drug containing acetaminophen (prescription or nonprescription). If you are not sure whether a drug contains acetaminophen, ask a doctor or pharmacist
• if you have ever had an allergic reaction to this product or any of its ingredients

Ask a doctor before use if you have
• liver disease
• glaucoma
• difficulty in urination due to enlargement of the prostate gland
• a breathing problem such as emphysema or chronic bronchitis

Ask a doctor or pharmacist before use if you are
• taking the blood thinning drug warfarin
• taking sedatives or tranquilizers

When using this product
• you may get drowsy
• avoid alcoholic drinks
• excitability may occur, especially in children
• alcohol, sedatives, and tranquilizers may increase drowsiness
• be careful when driving a motor vehicle or operating machinery
• limit the use of caffeine-containing medications, foods, or beverages beacuse too much caffeine may cause nervousness, irritability, sleeplessness, and, occasionally, rapid heartbeat. The recommended dose of this product contains about as much caffeine as a cup of coffee.

Stop use and ask a doctor if
• new symptoms occur
• redness or swelling is present
• pain gets worse or lasts more than 10 days
• fever gets worse or lasts more than 3 days

If pregnant or breast-feeding, ask a health professional before use

Keep out of reach of children.
Overdose warning: In case of overdose, get medical help or contact a Poison Control Center right away. Prompt medical attention is critical for adults as well as children even if you do not notice any signs or symptoms.

Directions

• do not take more than the recommended dose
• adults and children 12 years and older: take 2 gelcaps with water
• repeat every 6 hours as needed
• do not exceed 6 gelcaps per day
• children under 12 years: consult a doctor

Other information

• each gelcap contains: sodium 3 mg • store at room temperature.

Inactive ingredients

croscarmellose sodium, D&C red #33 aluminum lake, edible black printing ink, ethyl cellulose, FD&C blue #1 aluminum lake, gelatin, glycerin, hydroxypropyl methylcellulose, isopropyl alcohol, magnesium stearate, microcrystalline cellulose, pregelatinized potato starch, purified water, PVPK-30, sorbitol sorbitan solution, talc, titanium dioxide, triacetin

Questions or comments?

1-888-577-8033 Monday - Friday 8am - 4pm EST

Compare to the active ingredients in Midol® Complete††

Aspirin Free

• Relieves cramps, bloating, fatigue, headaches & backaches

READ AND KEEP OUTER CARTON FOR COMPLETE WARNINGS AND PRODUCT INFORMATION

TAMPER EVIDENT: Do not use if package is opened or if blister unit is torn, broken or shows any sign of tampering.

DISTRIBUTED BY: WALGREEN CO.
DEERFIELD, IL 60015
100% SATISFACTION GUARANTEED
walgreens.com 1-800-925-4733

©2023 Walgreen Co.

PRODUCT OF UNITED ARAB EMIRATES
PACKAGED AND QUALITY ASSURED IN THE U.S.A.

††Our pharmacists recommend the Walgreens brand. We invite you to compare to national brands.
††This product is not manufactured or distributed by Bayer HealthCare LLC, owner of the registered trademark Midol®.